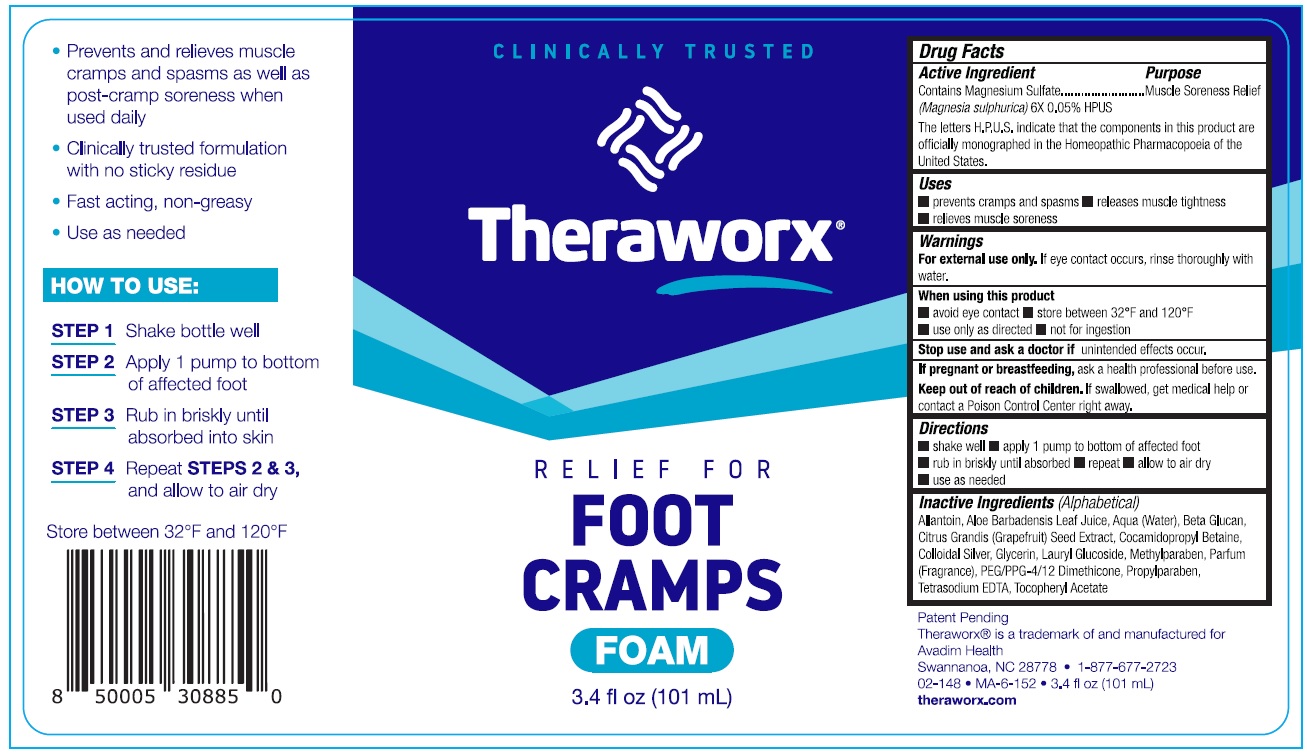 DRUG LABEL: Theraworx Relief for Foot Cramps Foam
NDC: 61594-021 | Form: AEROSOL, FOAM
Manufacturer: AVADIM HOLDINGS, INC.
Category: homeopathic | Type: HUMAN OTC DRUG LABEL
Date: 20230425

ACTIVE INGREDIENTS: MAGNESIUM SULFATE, UNSPECIFIED FORM 6 [hp_X]/1 mL
INACTIVE INGREDIENTS: ALLANTOIN; ALOE VERA LEAF; WATER; CITRUS MAXIMA SEED; COCAMIDOPROPYL BETAINE; SILVER; GLYCERIN; LAURYL GLUCOSIDE; METHYLPARABEN; PEG/PPG-4/12 DIMETHICONE; PROPYLPARABEN; EDETATE SODIUM; .ALPHA.-TOCOPHEROL ACETATE

Theraworx Relief for Foot Cramps Foam

Active Ingredient

Contains Magnesium Sulfate (Magnesia sulphurica) 6X 0.05% HPUS

The letters H.P.U.S. indicate that the components in this product are officially monographed in the Homeopathic Pharmacopoeia of the United States.

Purpose

Muscle Soreness Relief

Uses

- prevents cramps and spasms
- releases muscle tightness
- relieves muscle sorenss

Warnings

For external use only. If eye contact occurs, rinse thoroughly with water.

When using this product

- avoid eye contact
- store between 32ºF and 120ºF
- ues only as directed
- not for ingestion

Stop use and ask a doctor if

unintended effects occurs.

If pregnant or breastfeeding,

ask a health professional before use.

Keep out of reach of chidlren.

If swallowed, get medical help or contact a Poison Control right away.

Directions

- shake well
- apply 1 pump to bottom of affected foot
- rub in briskly until absorbed
- repeat
- allow to air dry
- use as needed

Inactive Ingredients (Alphabetical)

Allantoin, Aloe Barbadensis Leaf Extract, Aqua (Water), Beta Glucan, Citrus Grandis (Grapefruit) Seed Extract, Cocamidopropyl Betaine, Colloidal Silver, Glycerin, Lauryl Glucoside, Methylparaben, Parfum (Fragrance), PEG/PPG-4/12 Dimethicone, Propylparaben, Tetrasodium EDTA, Tocopheryl Acetate